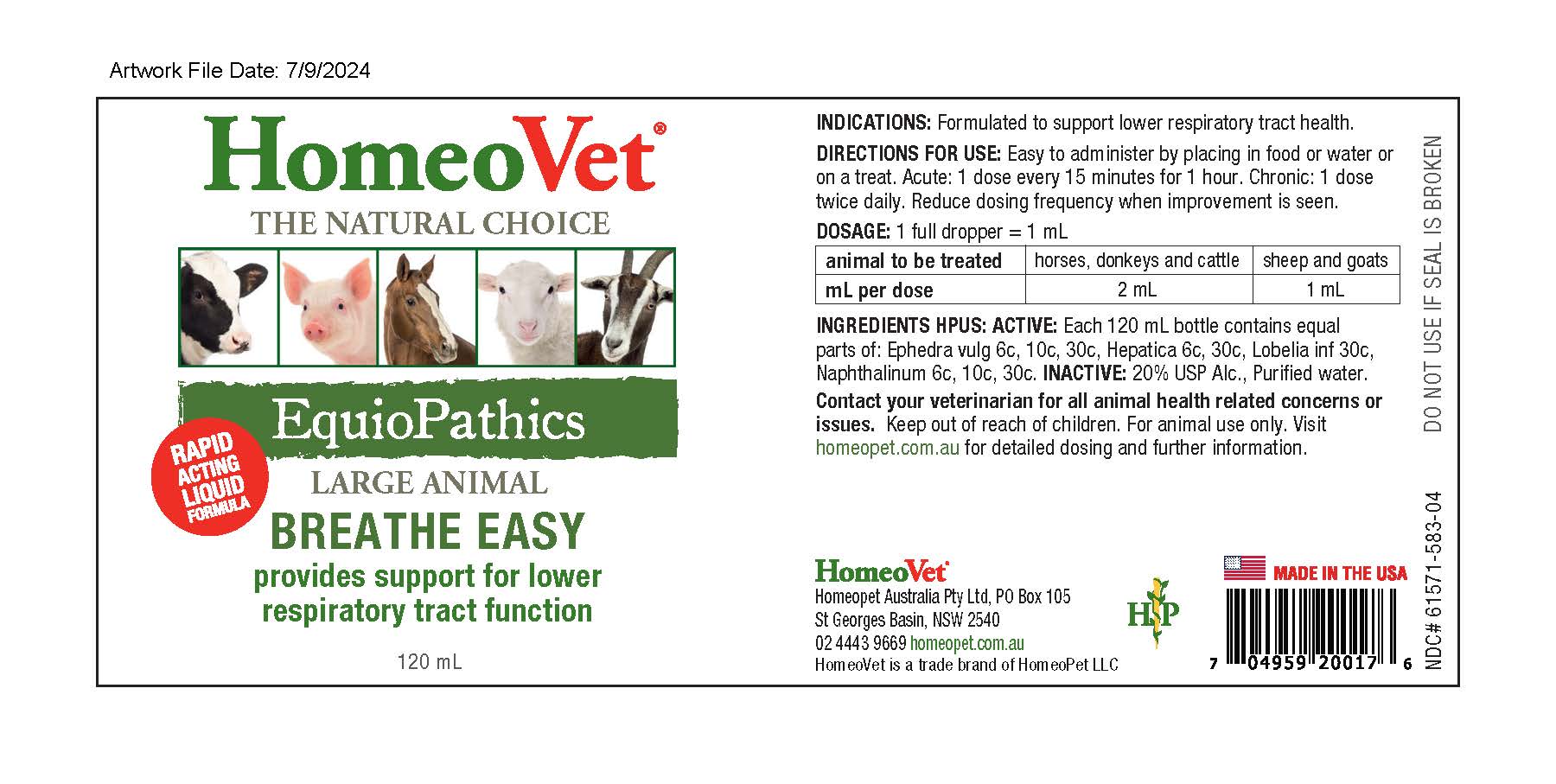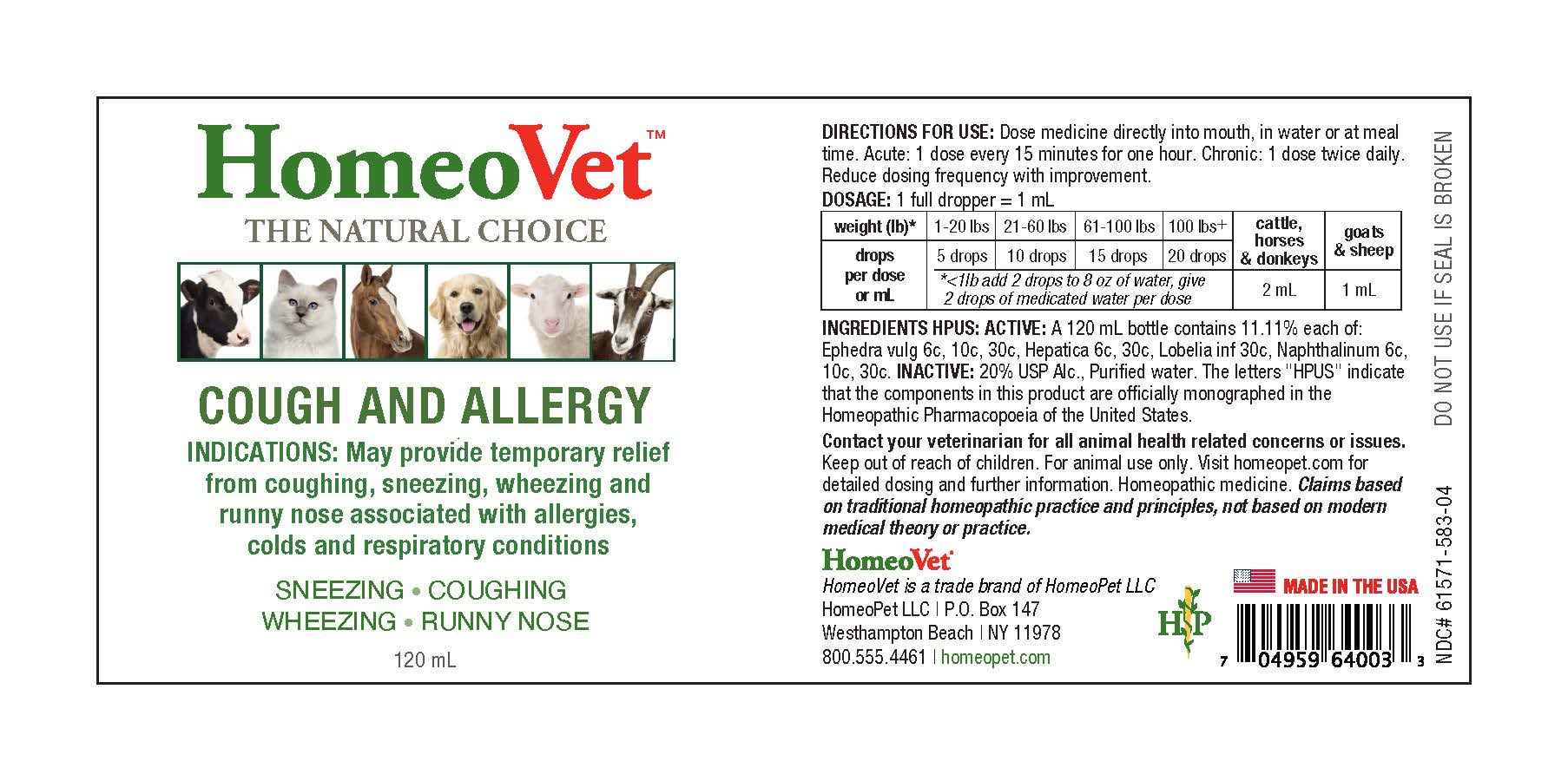 DRUG LABEL: Equiopathics Cough and Allergy
NDC: 61571-583 | Form: LIQUID
Manufacturer: HomeoPet, LLC
Category: homeopathic | Type: OTC ANIMAL DRUG LABEL
Date: 20251222

ACTIVE INGREDIENTS: EPHEDRA DISTACHYA FLOWERING TWIG 6 [hp_C]/120 mL; ANEMONE HEPATICA VAR. OBTUSA 6 [hp_C]/120 mL; LOBELIA INFLATA 30 [hp_C]/120 mL; NAPHTHALENE 6 [hp_C]/120 mL
INACTIVE INGREDIENTS: ALCOHOL; WATER

Cough and Allergy

INDICATIONS

May provide temporary relief from coughing, sneezing, wheezing and runny nose associated with allergies, colds and respiratory conditions.

SNEEZING - COUGHING - WHEEZING - RUNNY NOSE

ACTIVE INGREDIENT

Ephedra Vulgaris 6c,10c,30c, Hepatica Triloba 6c,30c,
Lobelia Inflata 30c, Naphthalinum 6c,10c,30c

INACTIVE

USP Alcohol and Purified Water

DIRECTIONS FOR USE

Dose medicine directly into mouth in water or at meal time. Acute: 1 dose every 15 minutes for one hour. Chronic: 1 dose twice daily. Reduce dosing frequency with improvement.

weight (lb)* | 1-20 lbs | 21-60 lbs | 61-100 lbs | 100 lbs+ | cattle, horses, & donkeys | goats & sheep
drops per dose or mL | 5 drops | 10 drops | 15 drops | 20 drops | 2 mL | 1 mL
drops per dose or mL | *<1 lb add 2 drops to 8 oz of water, give 2 drops of medicated water per dose |  |  |  | 2 mL | 1 mL

ASK DOCTOR

Contact your veterinarian for all animal health related concerns or issues. Keep out of reach of children. For animal use only. Visit homeopet.com for detailed dosing and further information. Homeopathic medicine. Claims based on traditional homeopathic practice and principles, not based on modern medical theory or practice.